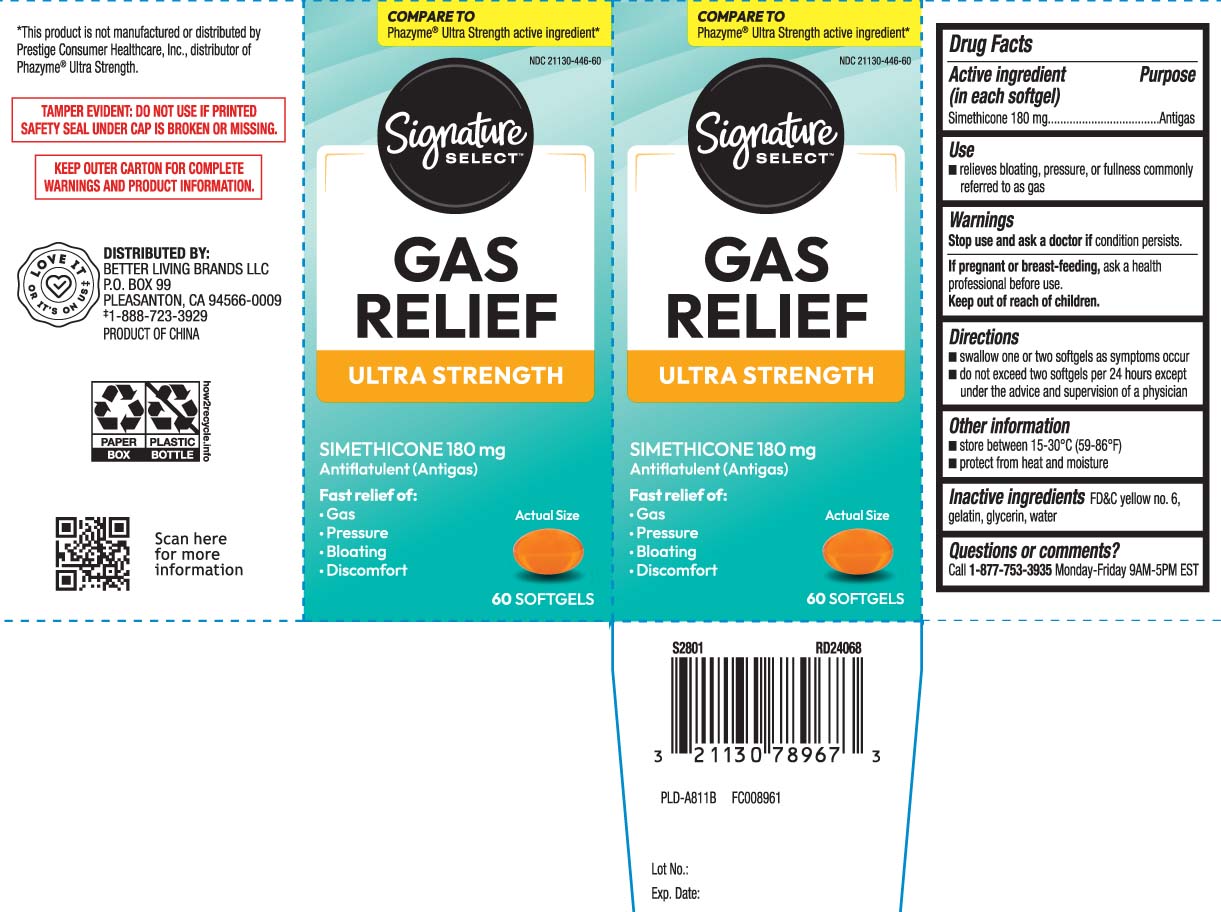 DRUG LABEL: Gas Relief
NDC: 21130-446 | Form: CAPSULE, LIQUID FILLED
Manufacturer: Safeway, Inc.
Category: otc | Type: HUMAN OTC DRUG LABEL
Date: 20260105

ACTIVE INGREDIENTS: DIMETHICONE 180 mg/1 1
INACTIVE INGREDIENTS: FD&C YELLOW NO. 6; GELATIN; GLYCERIN; WATER

Drug Facts

Active ingredient (in each softgel)

Simethicone 180 mg

Purpose

Antigas

Uses

- relieves bloating, pressure, or fullness commonly referred to as gas

Warnings

Stop use and ask a doctor if

condition persists

If pregnant or breast-feeding,

ask a health professional before use.

Directions

- swallow one or two softgels as symptoms occur
- do not exceed two softgels per 24 hours except under the advice and supervision of a physician

Other information

- store between 15-30°C (59-86°F)
- protect from heat and moisture

Inactive ingredients

FD&C yellow #6, gelatin, glycerin, water

Questions or comments?

Call 1-877-753-3935 Monday-Friday 9AM-5PM EST

Principal Display Panel

COMPARE TO Phazyme® Ultra Strength active ingredient*

GAS RELIEF

ULTRA STRENGTH

SIMETHICONE 180 mg

Antiflatulent (Antigas)

Fast relief of:

- Gas
- Pressure
- Bloating
- Discomfort

Softgels

*This product is not manufactured or distributed by Prestige Consumer Healthcare, Inc., distributor of Phazyme® Ultra Strength.

TAMPER EVIDENT: DO NOT USE IF PRINTED SAFETY SEAL UNDER CAP IS BROKEN OR MISSING.

KEEP OUTER CARTON FOR COMPLETE WARNINGS AND PRODUCT INFORMATION.

DISTRIBUTED BY

BETTER LIVING BRANDS LLC

P.O. BOX 99, PLEASANTON, CA 94566-0009

Package Label

SIGNATURE SELECT Gas Relief